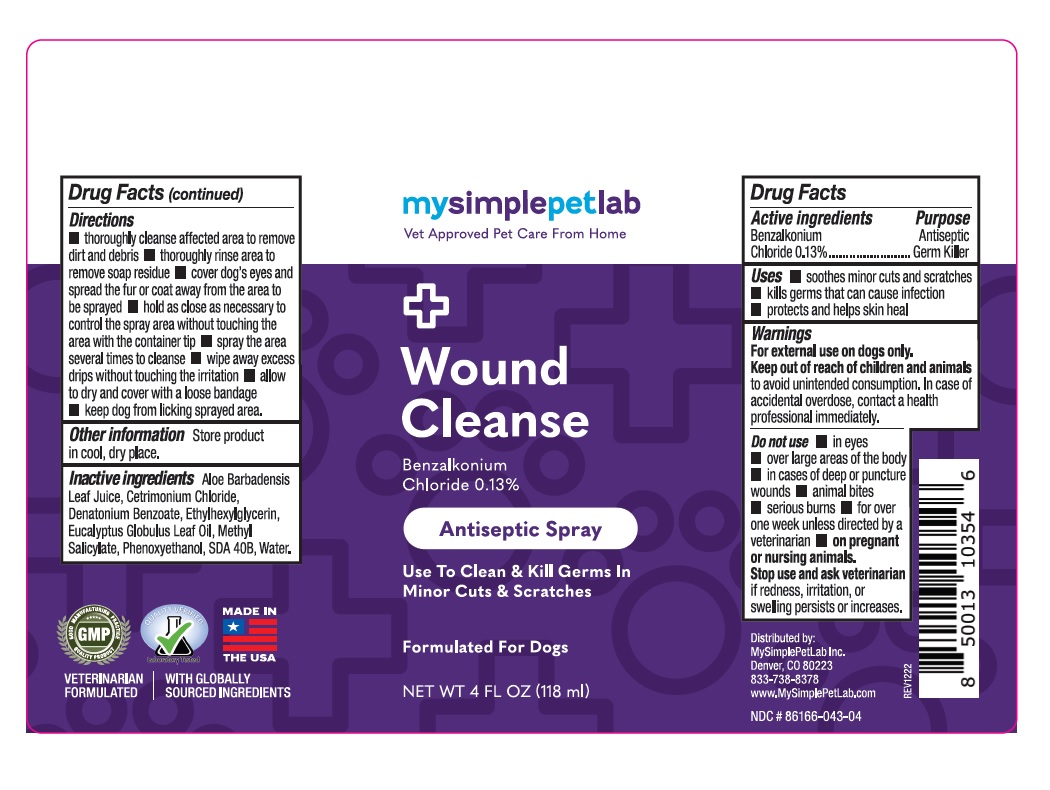 DRUG LABEL: MySimplePetLab Wound Cleanse
NDC: 86166-043 | Form: SPRAY
Manufacturer: Mysimplepetlab Inc
Category: animal | Type: OTC ANIMAL DRUG LABEL
Date: 20221201

ACTIVE INGREDIENTS: BENZALKONIUM CHLORIDE 0.13 g/100 mL
INACTIVE INGREDIENTS: ALOE VERA LEAF; CETRIMONIUM CHLORIDE; DENATONIUM BENZOATE; ETHYLHEXYLGLYCERIN; EUCALYPTUS OIL; METHYL SALICYLATE; PHENOXYETHANOL; ALCOHOL; WATER

mysimplepetlab Wound Cleanse

Active ingredients

Benzalkonium Chloride 0.13%

Purpose

Antiseptic Germ killer

Uses

• soothes minor cuts and scratches
• kills germs that can cause infection
• protects and helps skin heal

Warnings

For external use on dogs only.
Keep out of reach of children and animals to avoid unintended consumption. In case of accidental overdose, contact a health professional immediately.

Do not use • in eyes • over large areas of the body • in cases of deep or puncture wounds • animal bites • serious burns • for over one week unless directed by a veterinarian • on pregnant or nursing animals.
Stop use and ask veterinarian if redness, irritation, or swelling persists or increases.

Directions

• thoroughly cleanse affected area to remove dirt and debris • thoroughly rinse area to remove soap residue • cover dog’s eyes, spread the fur or coat away from the area to be sprayed • hold as close as necessary to control the spray area without touching the area with the container tip • spray the area several times to cleanse • wipe away excess drips without touching the irritation • allow to dry and cover with a loose bandage • keep dog from licking sprayed area.

Other information

Store product in cool, dry place.

Inactive ingredients

Aloe Barbadensis Leaf Juice, Cetrimonium Chloride, Denatonium Benzoate, Ethylhexylglycerin, Eucalyptus Globulus Leaf Oil, Methyl Salicylate, Phenoxyethanol, SDA 40B, Water.

Vet Approved Pet Care From Home

Use To Clean & Kill Germs In Minor Cuts & Scratches

Formulated for Dogs

MADE IN THE USA

VETERINARIAN FORMULATED | WITH GLOBALLY SOURCED INGREDIENTS

Distributed by:
MySimplePetLab Inc.
Denver, CO 80223
833-738-8378
www.MySimplePetLab.com